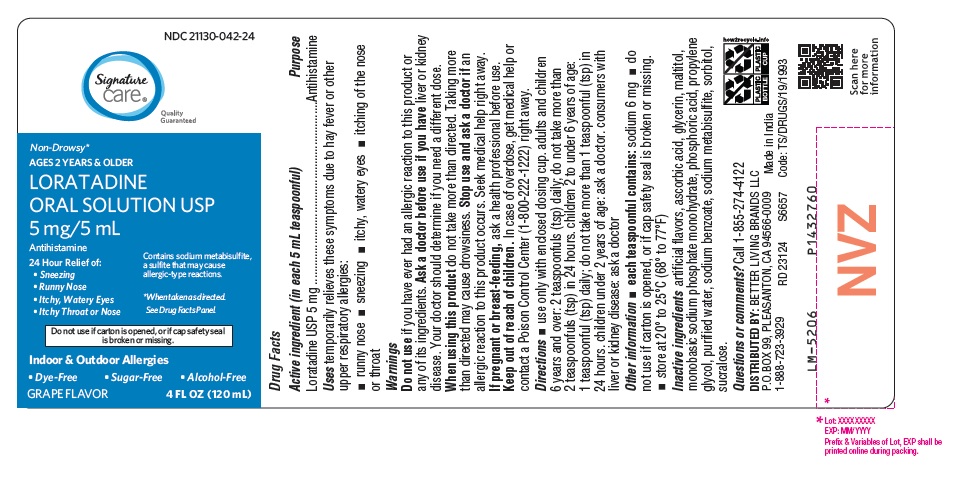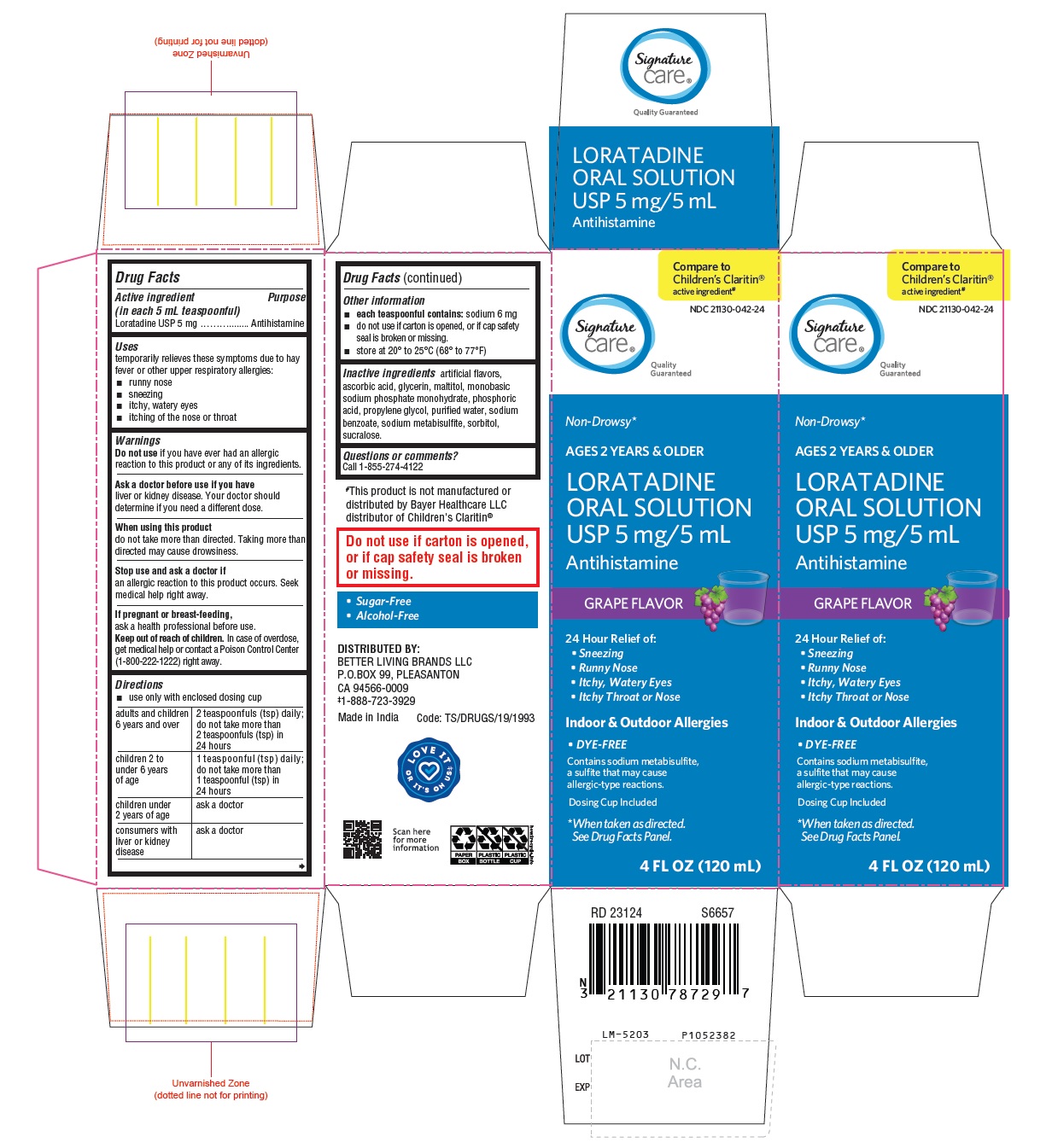 DRUG LABEL: Loratadine
NDC: 21130-042 | Form: SOLUTION
Manufacturer: Better Living Brands LLC
Category: otc | Type: Human OTC Drug Label
Date: 20230926

ACTIVE INGREDIENTS: LORATADINE 5 mg/5 mL
INACTIVE INGREDIENTS: GRAPE; ASCORBIC ACID; GLYCERIN; MALTITOL; SODIUM PHOSPHATE, MONOBASIC, MONOHYDRATE; PHOSPHORIC ACID; PROPYLENE GLYCOL; WATER; SODIUM BENZOATE; SODIUM METABISULFITE; SORBITOL; SUCRALOSE

Loratadine Oral Solution USP 5 mg/5 mL

Drug Facts

Active ingredient (in each 5 mL teaspoonful)
Loratadine USP 5 mg

Purpose

Antihistamine

Uses

temporarily relieves these symptoms due to hay fever or other upper respiratory allergies:

- runny nose
- sneezing
- itchy, watery eyes
- itching of the nose or throat

Warnings

Do not use if you have ever had an allergic reaction to this product or any of its ingredients.

Ask a doctor before use if you have

liver or kidney disease. Your doctor should determine if you need a different dose.

When using this product

do not take more than directed. Taking more than directed may cause drowsiness.

Stop use and ask a doctor if

an allergic reaction to this product occurs. Seek medical help right away.

If pregnant or breast-feeding,

ask a health professional before use.

Keep out of reach of children.

In case of overdose, get medical help or contact a Poison Control Center (1-800-222-1222) right away.

Directions

- use only with enclosed dosing cup

adults and children 6 years and over | 2 teaspoonfuls (tsp) daily; do not take more than 2 teaspoonfuls (tsp) in 24 hours
children 2 to under 6 years of age | 1 teaspoonful (tsp) daily; do not take more than 1 teaspoonful (tsp) in 24 hours
children under 2 years of age | ask a doctor
consumers with liver or kidney disease | ask a doctor

Other information

- each teaspoonful contains: sodium 6 mg
- do not use if carton is opened, or if cap safety seal is broken or missing.
- store at 20° to 25°C (68° to 77°F)

Inactive ingredients

artificial flavors, ascorbic acid, glycerin, maltitol, monobasic sodium phosphate monohydrate, phosphoric acid, propylene glycol, purified water, sodium benzoate, sodium metabisulfite, sorbitol, sucralose.

Questions or comments?

1-855-274-4122
DISTRIBUTED BY:
BETTER LIVING BRANDS LLC
P.O.BOX 99
PLEASANTON, CA 94566-0009
‡1-888-723-3929
Made in India
Code:TS/DRUGS/19/1993

PACKAGE LABEL-PRINCIPAL DISPLAY PANEL - 5 mg/5 mL (120 mL Bottle)

NDC 21130-042-24
Signature
care®
Quality Guaranteed
Non-Drowsy*
AGES 2 YEARS & OLDER

LORATADINE
ORAL SOLUTION USP
5 mg/5 mL

Antihistamine
24 Hour Relief of:
• Sneezing
• Runny Nose
• Itchy, Watery Eyes
• Itchy Throat or Nose
Contains sodium metabisulfite,
a sulfite that may cause
allergic-type reactions.
*When taken as directed.
See Drug Facts Panel.
Do not use if carton is opened, or if cap safety seal
is broken or missing.
Indoor & Outdoor Allergies
• Dye-Free • Sugar-Free • Alcohol-Free
GRAPE FLAVOR 4 FL OZ (120 mL)

PACKAGE LABEL-PRINCIPAL DISPLAY PANEL - 5 mg/5 mL Carton (120 mL)

Compare to
Children's Claritin®
active ingredient

NDC 21130-042-24
Signature
care®
Quality Guaranteed
Non-Drowsy*
AGES 2 YEARS & OLDER

LORATADINE
ORAL SOLUTION
USP 5 mg/5 mL

Antihistamine
GRAPE FLAVOR
24 Hour Relief of:
• Sneezing
• Runny Nose
• Itchy, Watery Eyes
• Itchy Throat or Nose
Indoor & Outdoor Allergies
• DYE-FREE
Contains sodium metabisulfite,
a sulfite that may cause
allergic-type reactions.
Dosing Cup Included
*When taken as directed.
See Drug Facts Panel.
4 FL OZ (120 mL)